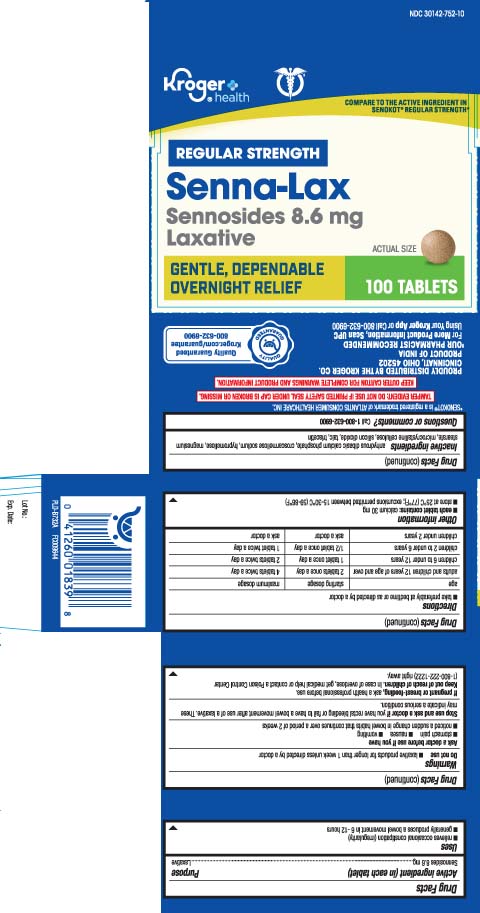 DRUG LABEL: Senna Laxative
NDC: 30142-752 | Form: TABLET
Manufacturer: The Kroger Co.
Category: otc | Type: HUMAN OTC DRUG LABEL
Date: 20251201

ACTIVE INGREDIENTS: SENNOSIDES 8.6 mg/1 1
INACTIVE INGREDIENTS: CROSCARMELLOSE SODIUM; ANHYDROUS DIBASIC CALCIUM PHOSPHATE; HYPROMELLOSES; MAGNESIUM STEARATE; TALC; CELLULOSE, MICROCRYSTALLINE; TRIACETIN; SILICON DIOXIDE

Drug Facts

Active ingredient (in each tablet)

Sennosides 8.6 mg

Purpose

Laxative

Uses

- relieves occasional constipation (irregularity)
- generally produces a bowel movement in 6-12 hours

Warnings

Do not use

- laxative products for longer than 1 week unless directed by a doctor

Ask a doctor before use if you have

- stomach pain
- nausea
- vomiting
- noticed a sudden change in bowel habits that continues over a periodof 2 weeks

Stop use and ask a doctor if

you have rectal bleeding or fail to have a bowel movement after use of a laxative. These may indicate a serious condition.

If pregnant or breast-feeding,

ask a health professional before use.

Keep out of reach of children.

In case of overdose, get medical help or contact a Poison Control Center (1-800-222-1222) right away.

Directions

- take preferably at bedtime or as directed by a doctor

age | starting dosage | maximum dosage
adults and children 12 years of age and over | 2 tablets once a day | 4 tablets twice a day
children 6 to under 12 years | 1 tablet once a day | 2 tablets twice a day
children 2 to under 6 years | 1/2 tablet once a day | 1 tablet twice a day
children under 2 years | ask a doctor | ask a doctor

Other information

- each tablet contains: calcium 30 mg
- store at 25ºC (77ºF); excursions permitted between 15-30ºC (59-86ºF)

Inactive ingredients

croscarmellose sodium, anhydrous dibasic calcium phosphate dihydrate, hypromellose, magnesium stearate, microcrystalline cellulose, silicon dioxide, talc, triacetin

Questions or comments?

Call 1-800-632-6900

Principal Display Panel

COMPARE TO THE ACTIVE INGREDIENT IN SENOKOT® REGULAR STRENGTH*

REGULAR STRENGTH

Senna-Lax

Sennosides 8.6 mg

Laxative

GENTLE, DEPENDABLE OVERNIGHT RELIEF

TABLETS

*Senokot® is a registered trademark of ATLANTIS CONSUMER HEALTHCARE INC.

TAMPER EVIDENT: DO NOT USE IF PRINTED SAFETY SEAL UNDER CAP IS BROKEN OR MISSING.

KEEP OUTER CARTON FOR COMPLETE WARNINGS AND PRODUCT INFORMATION.

DISTRIBUTED BY THE KROGER CO.

CINCINNATI, OHIO 45202

Product Labeling

KROGER HEALTH Regular Strength Senna-Lax